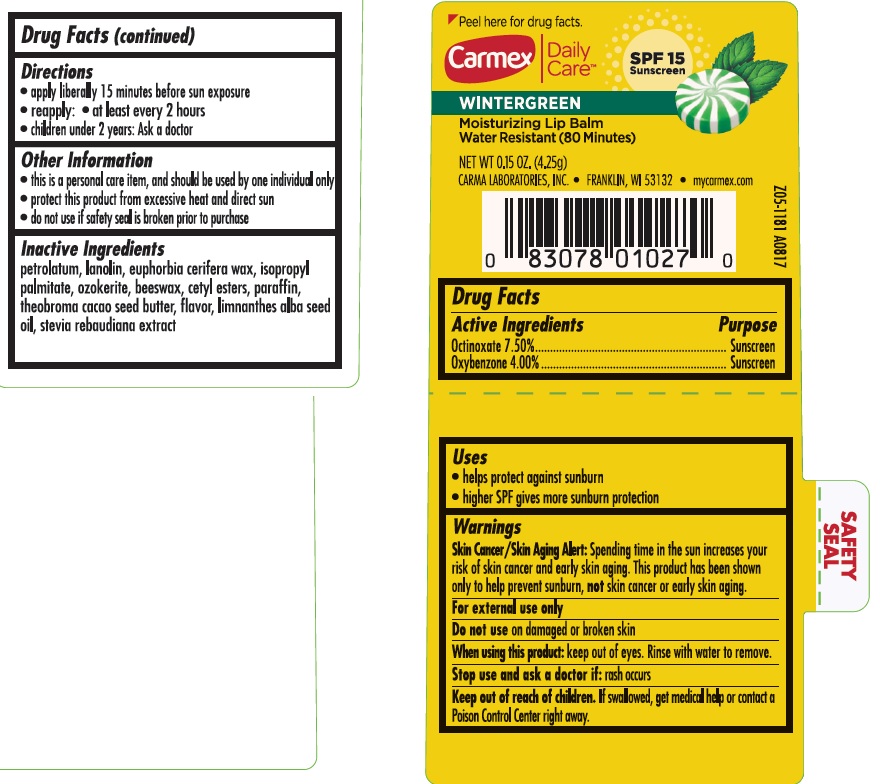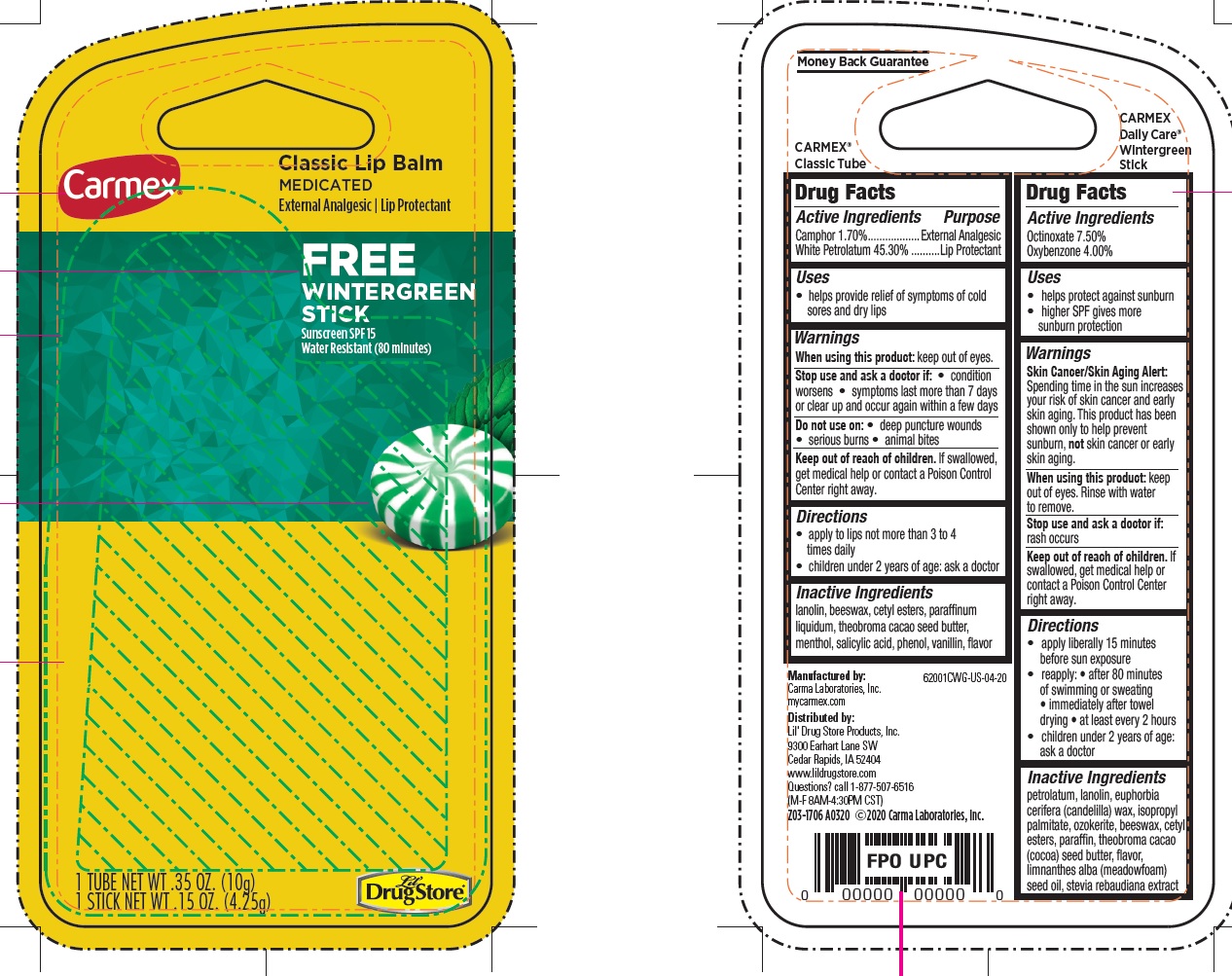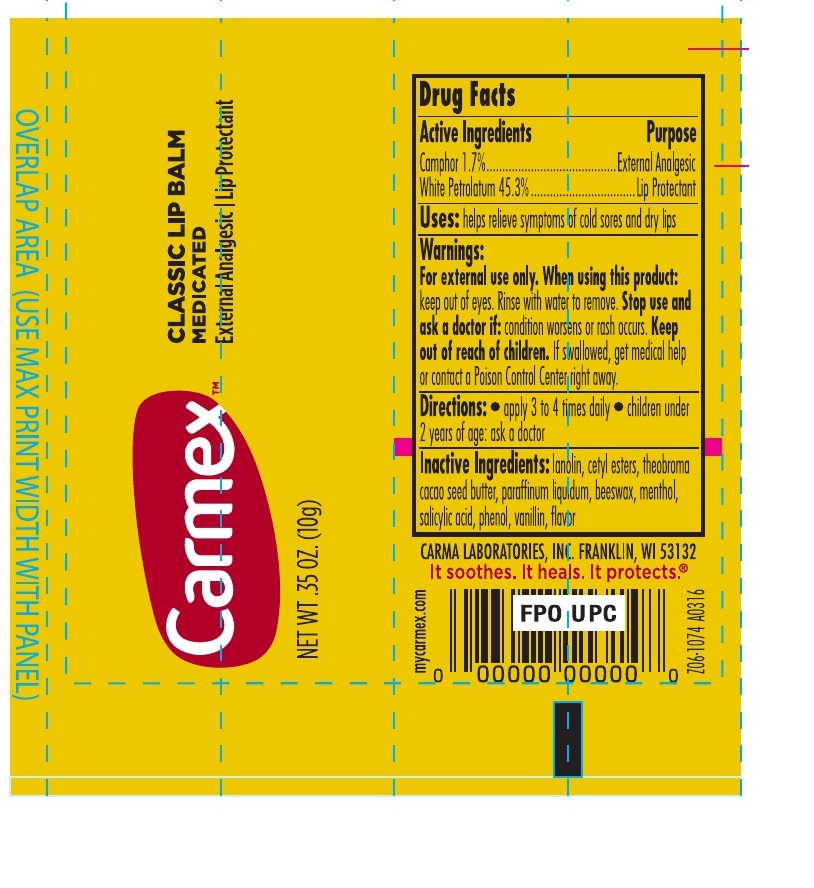 DRUG LABEL: Carmex Classic Lip Balm Medicated Free Wintergreen Stick
NDC: 10210-0047 | Form: KIT | Route: TOPICAL
Manufacturer: Carma Laboratories, Inc.
Category: otc | Type: HUMAN OTC DRUG LABEL
Date: 20231208

ACTIVE INGREDIENTS: OCTINOXATE 75 mg/1 g; OXYBENZONE 40 mg/1 g; CAMPHOR (SYNTHETIC) 17 mg/1 g; WHITE PETROLATUM 453 mg/1 g
INACTIVE INGREDIENTS: PETROLATUM; LANOLIN; ISOPROPYL PALMITATE; CERESIN; YELLOW WAX; CETYL ESTERS WAX; PARAFFIN; MEADOWFOAM SEED OIL; LANOLIN; YELLOW WAX; CETYL ESTERS WAX; MINERAL OIL; MENTHOL; SALICYLIC ACID; PHENOL; VANILLIN

Carmex Classic Lip Balm Medicated Free Wintergreen Stick, kit

Active Ingredients

Octinoxate 7.50%

Oxybenzone 4.00%

Uses

• helps protect against sunburn
• higher SPF gives more sunburn protection

Warnings

Skin Cancer/Skin Aging Alert: Spending time in the sun increases your risk of skin cancer and early skin aging. This product has been shown only to help prevent sunburn, not skin cancer or early skin aging.

When using this product:

keep out of eyes. Rinse with water to remove.

Stop use and ask a doctor if:

rash occurs

Keep out of reach of children.

If swallowed, get medical help or contact a Poison Control Center right away.

Directions

• apply liberally 15 minutes before sun exposure
• reapply: • after 80 minutes of swimming or sweating • immediately after towel drying
• at least every 2 hours
• children under 2 years of age: ask a doctor

Inactive Ingredients

petrolatum, lanolin, euphorbia cerifera (candelilla) wax, isopropyl palmitate, ozokerite, beeswax, cetyl esters, paraffin, theobroma cacao (cocoa) seed butter, flavor, limnanthes alba (meadowfoam) seed oil, stevia rebaudiana extract

Active Ingredients

Camphor 1.70%

White Petrolatum 45.30%

Purpose

External Analgesic

Lip Protectant

Uses

- helps provide relief of symptoms of cold sores and dry lips

Warnings

When using this product:

keep out of eyes.

Stop use and ask a doctor if:

• condition worsens • symptoms last more than 7 days or clear up and occur again within a few days

Do not use on:

• deep puncture wounds • serious burns • animal bites

Keep out of reach of children.

If swallowed, get medical help or contact a Poison Control Center right away.

Directions

• apply to lips not more than 3 to 4 times daily
• children under 2 years of age: ask a doctor

Inactive Ingredients

lanolin, beeswax, cetyl esters, paraffinum liquidum, theobroma cacao seed butter, menthol, salicylic acid, phenol, vanillin, flavor